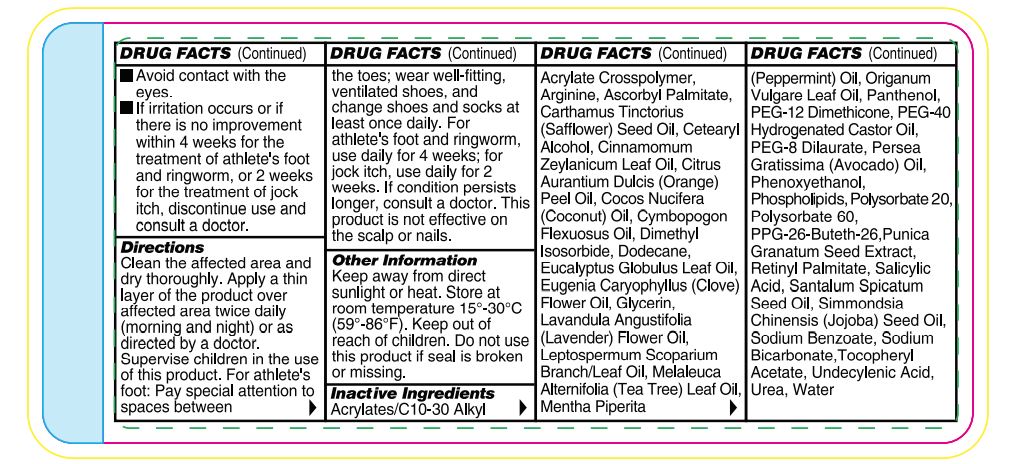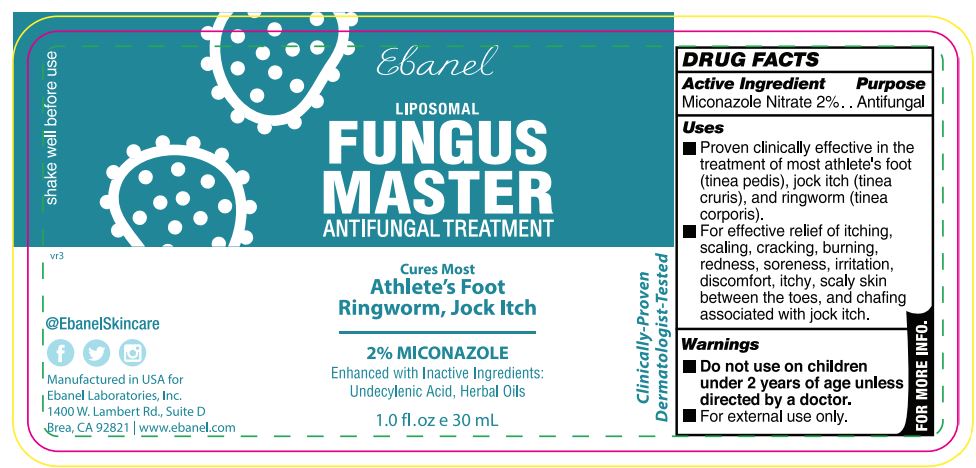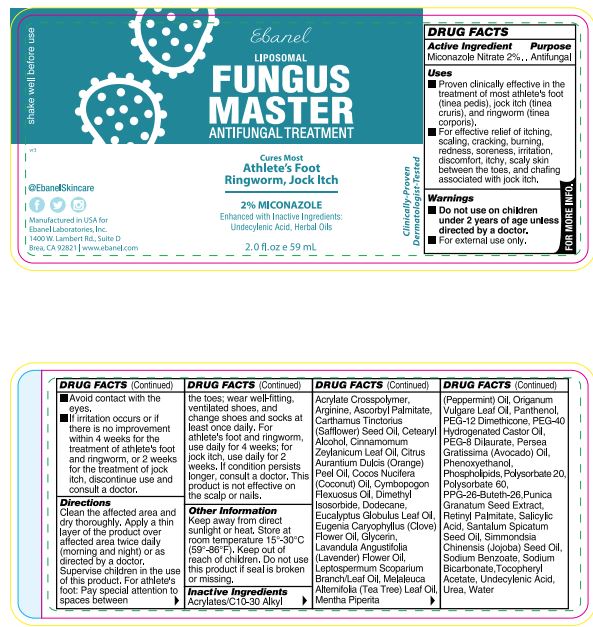 DRUG LABEL: Fungus Master Antifungal Treatment
NDC: 72654-001 | Form: LOTION
Manufacturer: Ebanel Laboratories, Inc
Category: otc | Type: HUMAN OTC DRUG LABEL
Date: 20260209

ACTIVE INGREDIENTS: MICONAZOLE NITRATE 20 mg/1 mL
INACTIVE INGREDIENTS: CARBOMER INTERPOLYMER TYPE A (ALLYL SUCROSE CROSSLINKED); ARGININE; ASCORBYL PALMITATE; SAFFLOWER OIL; CETOSTEARYL ALCOHOL; CINNAMON LEAF OIL; ORANGE OIL; COCONUT OIL; EAST INDIAN LEMONGRASS OIL; DIMETHYL ISOSORBIDE; DODECANE; EUCALYPTUS OIL; CLOVE OIL; GLYCERIN; MANUKA OIL; TEA TREE OIL; PEPPERMINT OIL; PANTHENOL; PEG-12 DIMETHICONE; POLYOXYL 40 HYDROGENATED CASTOR OIL; PEG-8 DILAURATE; AVOCADO OIL; PHENOXYETHANOL; LECITHIN, SOYBEAN; POLYSORBATE 20; POLYSORBATE 60; PPG-26-BUTETH-26; POMEGRANATE SEED; VITAMIN A PALMITATE; SALICYLIC ACID; JOJOBA OIL; SODIUM BENZOATE; SODIUM BICARBONATE; .ALPHA.-TOCOPHEROL ACETATE; UNDECYLENIC ACID; UREA; WATER

Fungus Master Antifungal Treatment

Active Ingredient

Miconazole Nitrate 2%

Purpose

Antifungal

Uses

- Proven clinically effective in the treatment of most athlete’s foot(Tinea Pedis), jock itch(Tinea Cruris) and ringworm(Tinea Corporis).
- For effective relief of itching, scaling, cracking, burning, redness, Soreness, irritation, discomfort, itchy, scaly skin between the toes, and chafing associated with jock itch.

Warnings

- Do not use on children under 2 years of age.
- For external use only.
- Avoid contact with the eyes.
- If irritation occurs or if there is no improvement within 4 weeks (for athlete’s foot and ringworm) or within 2 weeks (for jock itch), discontinue use and consult a doctor.

Keep out of reach of children.

If swallowed, get medical help or contact a poison control center right away.

Directions

Wash the affected area and dry thoroughly. Apply a thin layer of the product over affected area twice daily (morning and night) or as directed by a doctor. Supervise children in the use of this product. For athlete’s foot: Pay special attention to spaces between the toes; wear well-fitting, ventilated shoes, and change shoes and socks at least once daily. For athlete’s foot and ringworm use daily for 4 weeks; for jock itch, use daily for 2 weeks. If condition persists longer, consult a doctor. This product is not effective on the scalp or nails. Store at 15-30°C (59-86°F)

Other Information

Functional ingredients used in this formula have been shown to improve the appearance of thickened, discolored, and unhealthylooking feet caused by dermatophytic fungi. Urea has been shown to thin, soften, and act as penetrating agent on skin. Undecylenic acid is effective as an emulsifier, cleanser, and preservative.

Inactive Ingredients

Acrylates/C10-30 Alkyl Acrylate Crosspolymer, Arginine, Ascorbyl Palmitate, Carthamus Tinctorius (Safflower) Seed Oil, Cetearyl Alcohol, Cinnamomum Zeylanicum Leaf Oil, Citrus Aurantium Dulcis (Orange) Peel Oil, Cocos Nucifera (Coconut) Oil, Cymbopogon Flexuosus Oil, Dimethyl Isosorbide, Dodecane, Eucalyptus Globulus Leaf Oil, Eugenia Caryophyllus (Clove) Flower Oil, Glycerin, Lavandula Angustifolia (Lavender) Flower Oil, Leptospermum Scoparium Branch/Leaf Oil, Melaleuca Alternifolia (Tea Tree) Leaf Oil, Mentha Piperita (Peppermint) Oil, Oreganum Vulgare Leaf Oil, Panthenol, PEG-12 Dimethicone, PEG-40 Hydrogenated Castor Oil, PEG-8 Dilaurate, Persea Gratissima (Avocado) Oil, Phenoxyethanol, Phospholipids, Polysorbate 20, Polysorbate 60, PPG-26-Buteth-26, Punica Granatum Seed Extract, Retinyl Palmitate, Salicylic Acid, Santalum Spicatum Seed Oil, Simmondsia Chinensis (Jojoba) Seed Oil, Sodium Benzoate, Sodium Bicarbonate,Tocopheryl Acetate,Undecylenic Acid, Inact ive Ingredients Urea, Water